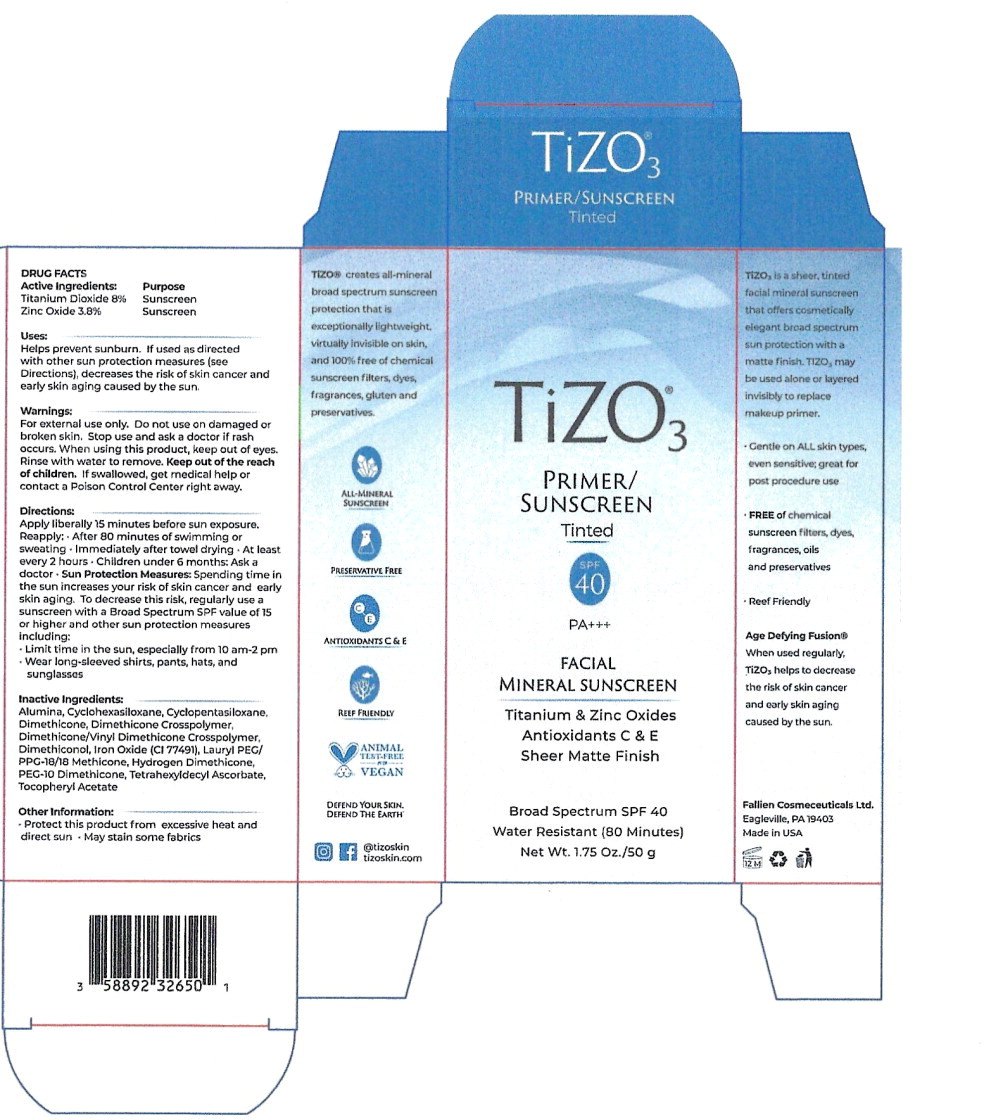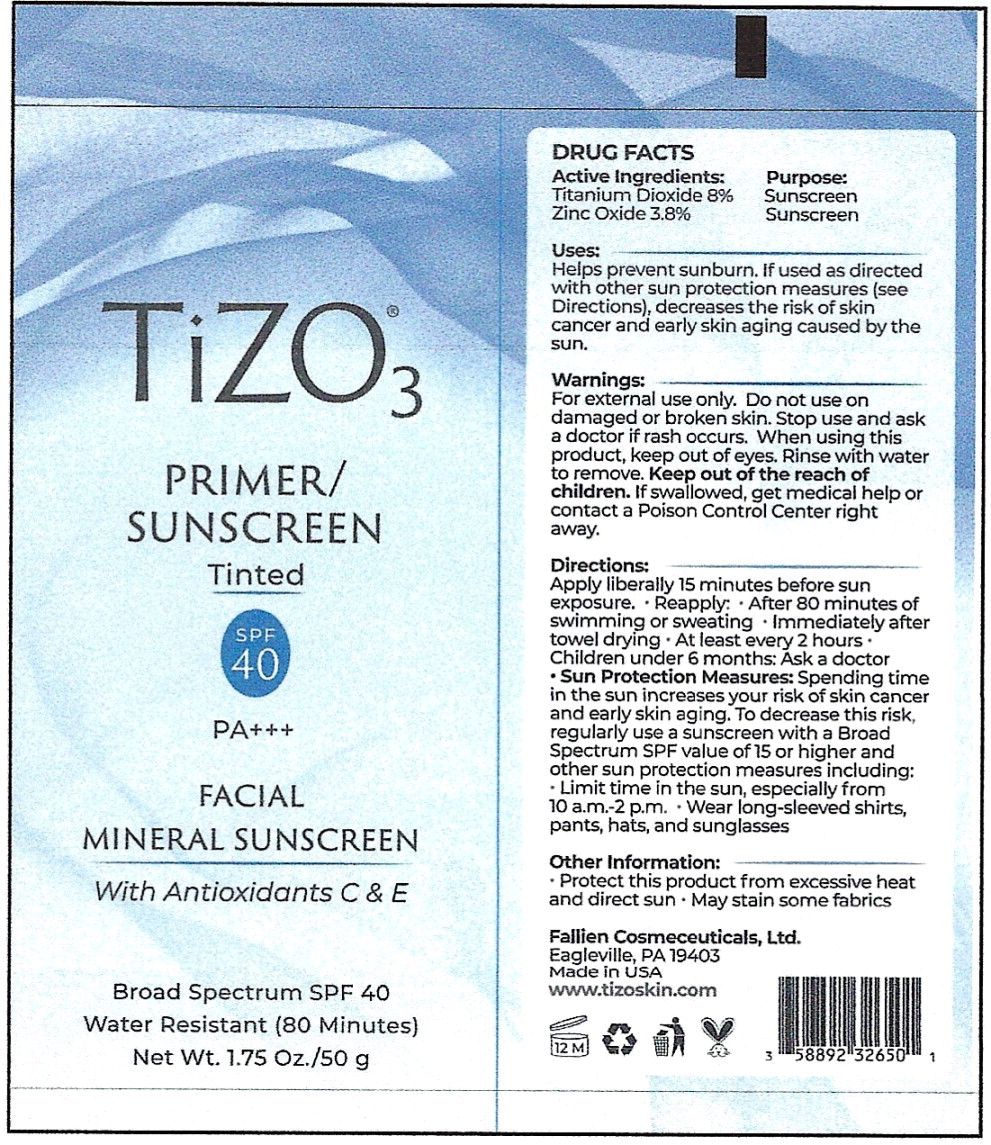 DRUG LABEL: TiZO3
NDC: 58892-326 | Form: CREAM
Manufacturer: Fallien Cosmeceuticals, LTD
Category: otc | Type: HUMAN OTC DRUG LABEL
Date: 20241001

ACTIVE INGREDIENTS: Titanium Dioxide 85.4 mg/1 mL; Zinc Oxide 40.7 mg/1 mL
INACTIVE INGREDIENTS: Aluminum Hydroxide; Cyclomethicone 6; Cyclomethicone 5; Dimethicone 20; Dimethicone Crosspolymer (450000 MPA.S AT 12% in Cyclopentasiloxane); Dimethicone/Vinyl Dimethicone Crosspolymer (Soft Particle); Dimethiconol (2000 CST); Brown Iron Oxide; Lauryl PEG/PPG-18/18 Methicone; Hydrogen Dimethicone (20 CST); PEG-10 Dimethicone (600 CST); Tetrahexyldecyl Ascorbate; .Alpha.-Tocopherol Acetate

DRUG FACTS

Active Ingredients:

Titanium Dioxide 8%

Zinc Oxide 3.8%

Purpose

Sunscreen

Sunscreen

Uses:

Helps prevent sunburn. If used as directed with other sun protection measures (see Directions), decreases the risk of skin cancer and early skin aging caused by the sun.

Warnings:

For external use only. Do not use on damaged or broken skin.

Stop use and ask a doctor if rash occurs.

When using this product keep out of eyes. Rinse with water to remove.

KEEP OUT OF REACH OF CHILDREN

Keep out of the reach of children. If swallowed, get medical help or contact a Poison Control Center right away.

Directions:

Apply liberally 15 minutes before sun exposure.

Reapply:

- After 80 minutes of swimming or sweating
- Immediately after towel drying.
- At least every 2 hours. Children under 6 months: Ask a doctor
- Sun Protection Measures: Spending time in the sun increases your risk of skin cancer and early skin aging. To decrease this risk, regularly use a sunscreen with a Broad Spectrum SPF value of 15 or higher and other sun protection measures including:
  - Limit lime in the sun, especially from 10 am-2 pm
  - Wear long-sleeved shirts, pants, hats, and sunglasses

Inactive Ingredients:

Alumina, Cyclohexasiloxane, Cyclopentasiloxane, Dimethicone, Dimethicone Crosspolymer, Dimethicone/Vinyl Dimethicone Crosspolymer, Dimethiconol, Iron Oxide (Cl 77491), Lauryl PEG/ PPG-18/18 Methicone, Hydrogen Dimethicone, PEG-10 Dimethicone, Tetrahexyldecyl Ascorbate, Tocopheryl Acetate

Other Information:

- Protect this product from excessive heat and direct sun - May stain some fabrics

Principal Display Panel - 50 g Carton Label

TiZO® 3

PRIMER/
SUNSCREEN

Tinted

SPF
40

PA+++

FACIAL
MINERAL SUNSCREEN

Titanium & Zinc Oxides

Antioxidants C & E

Sheer Matte Finish

Broad Spectrum SPF 40

Water Resistant (80 Minutes)

Net Wt. 1.75 Oz./50 g

Principal Display Panel - 50 g Tube Label

TiZO® 3

PRIMER/
SUNSCREEN

Tinted

SPF
40

PA+++

FACIAL
MINERAL SUNSCREEN

With Antioxidants C & E

Broad Spectrum SPF 40

Water Resistant (80 Minutes)

Net Wt. 1.75 Oz./50 g